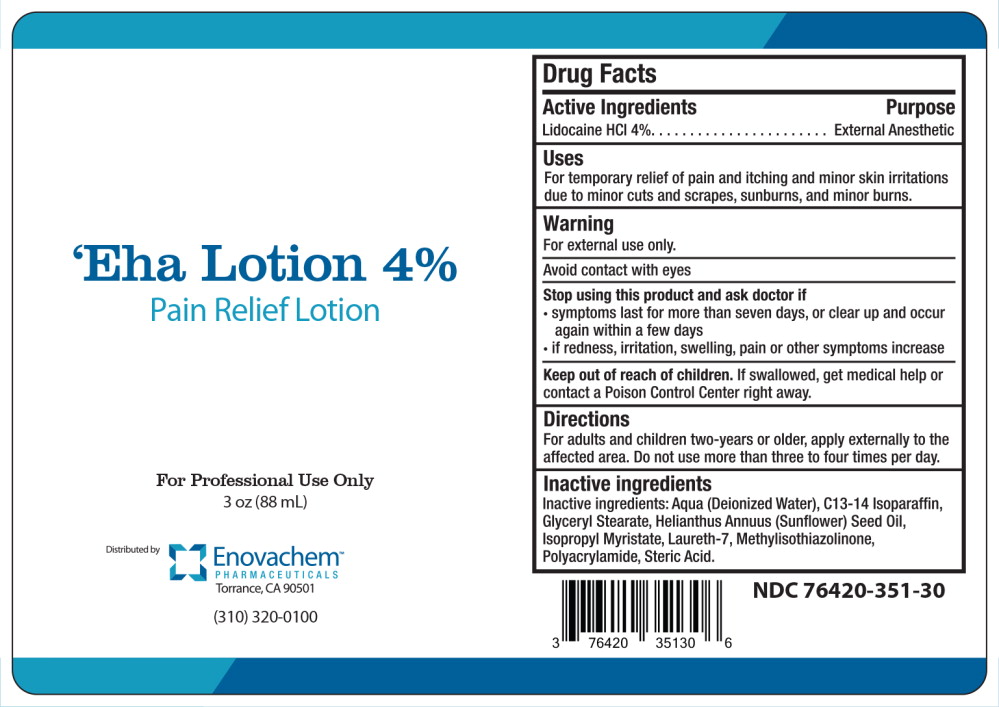 DRUG LABEL: Eha
NDC: 76420-351 | Form: LOTION
Manufacturer: Asclemed USA, Inc.
Category: prescription | Type: HUMAN PRESCRIPTION DRUG LABEL
Date: 20181101

ACTIVE INGREDIENTS: LIDOCAINE HYDROCHLORIDE 4 g/1 mL
INACTIVE INGREDIENTS: WATER; C13-14 ISOPARAFFIN; GLYCERYL MONOSTEARATE; HELIANTHUS ANNUUS FLOWERING TOP; ISOPROPYL MYRISTATE; LAURETH-7; METHYLISOTHIAZOLINONE; STEARIC ACID

Drug Facts

Active Ingredients

Lidocaine HCI 4%

Purpose

External Anesthetic

Uses

For temporary relief of pain and itching and minor skin irritations due to minor cuts and scrapes, sunburns, and minor burns.

Warning

For external use only.

Avoid contact with eyes

Stop using this product and ask doctor if

- symptoms last for more than seven days, or clear up and occur again within a few days
- if redness, irritation, swelling, pain or other symptoms increase

Keep out of reach of children. If swallowed, get medical help or contact a Poison Control Center right away.

Directions

For adults and children two-years or older, apply externally to the affected area. Do not use more than three to four times per day.

Inactive ingredients

Inactive ingredients: Aqua (Deionized Water), C13-14 Isoparaffin, Glyceryl Stearate, Helianthus Annuus (Sunflower) Seed Oil, Isopropyl Myristate, Laureth-7, M Polyacrylamide, Steric Acid.

Principal Display Panel - 88 mL Bottle Label

‘Eha Lotion 4%

Pain Relief Lotion

For Professional Use Only

3 OZ (88 mL)

Distributed by

Enovachem™

PHARMACEUTICALS

Torrance, CA 90501

(310) 320-0100